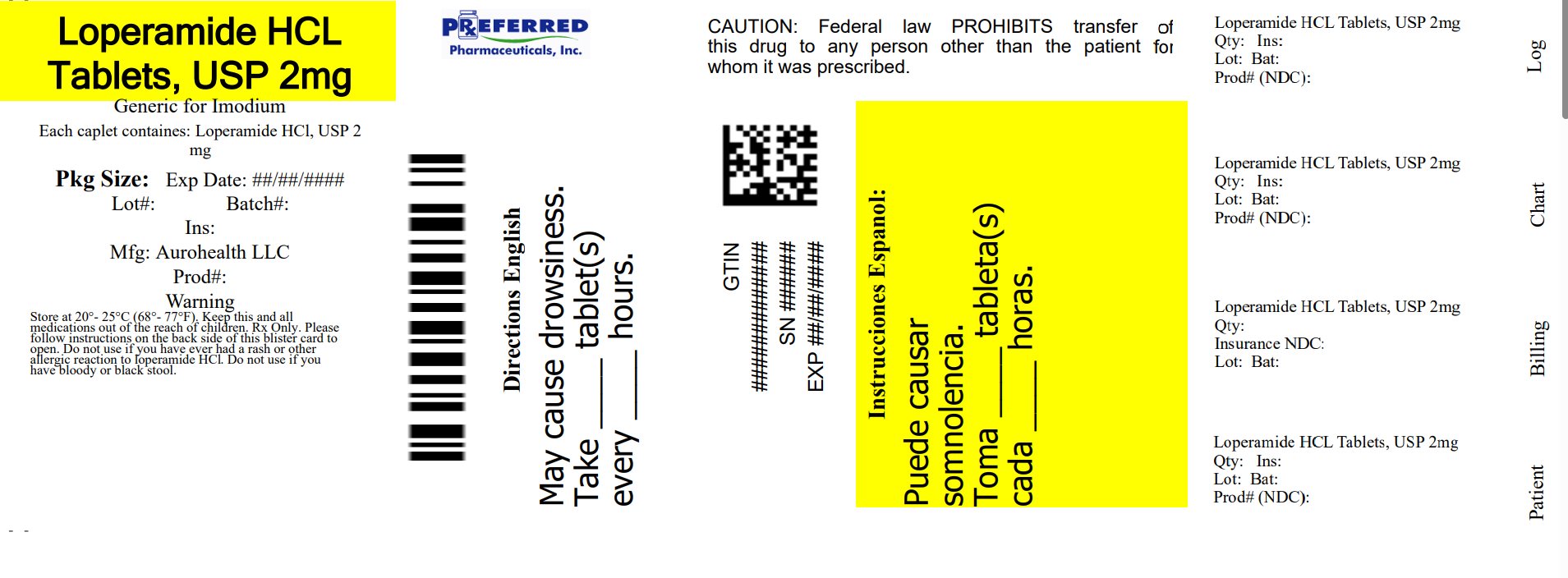 DRUG LABEL: Loperamide Hydrochloride
NDC: 68788-8393 | Form: TABLET
Manufacturer: Preferred Pharmaceuticals Inc.
Category: otc | Type: HUMAN OTC DRUG LABEL
Date: 20250723

ACTIVE INGREDIENTS: LOPERAMIDE HYDROCHLORIDE 2 mg/1 1
INACTIVE INGREDIENTS: SILICON DIOXIDE; D&C YELLOW NO. 10; FD&C BLUE NO. 1; LACTOSE MONOHYDRATE; MAGNESIUM STEARATE; MICROCRYSTALLINE CELLULOSE; SODIUM STARCH GLYCOLATE TYPE A POTATO

Drug Facts

Active ingredient (in each tablet)
Loperamide hydrochloride USP 2 mg

Purpose

Anti-diarrheal

Use

controls symptoms of diarrhea, including Travelers' Diarrhea

Warnings

Allergy alert: Do not use if you have ever had a rash or other allergic reaction to loperamide hydrochloride
Heart alert: Taking more than directed can cause serious heart problems or death

Do not use

if you have bloody or black stool

Ask a doctor before use if you have

- fever
- mucus in the stool
- a history of liver disease
- a history of abnormal heart rhythm

Ask a doctor or pharmacist before use if you are

taking a prescription drug. Loperamide may interact with certain prescription drugs.

When using this product

tiredness, drowsiness or dizziness may occur. Be careful when driving or operating machinery.

Stop use and ask a doctor if

- symptoms get worse
- diarrhea lasts for more than 2 days
- you get abdominal swelling or bulging. These may be signs of a serious condition.

If pregnant or breast-feeding,

ask a health professional before use.

Keep out of reach of children.

In case of overdose, get medical help or contact a Poison Control Center (1-800-222-1222) right away.

Directions

- drink plenty of clear fluids to help prevent dehydration caused by diarrhea
- find right dose on chart. If possible, use weight to dose; otherwise, use age.

adults and children 12 years and over | 2 tablets after the first loose stool; 1 tablet after each subsequent loose stool; but no more than 4 tablets in 24 hours
children 9 to 11 years (60 to 95 lbs) | 1 tablet after the first loose stool; 1/2 tablet after each subsequent loose stool; but no more than 3 tablets in 24 hours
children 6 to 8 years (48 to 59 lbs) | 1 tablet after the first loose stool; 1/2 tablet after each subsequent loose stool; but no more than 2 tablets in 24 hours
children 2 to 5 years (34 to 47 lbs) | ask a doctor
children under 2 years (up to 33 lbs) | do not use

Other information

- store at 20° to 25°C (68° to 77°F).
- do not use if carton or blister unit is open or torn
- Meets USP dissolution test 2
- See side panel for lot number and expiration date

Inactive ingredients

colloidal silicon dioxide, D & C yellow No. 10 aluminum lake, FD & C blue No. 1, lactose monohydrate, magnesium stearate, microcrystalline cellulose, and sodium starch glycolate

Questions or comments?

call 1-855-274-4122
Distributed by:
AUROHEALTH LLC
279 Princeton-Hightstown Road
East Windsor, NJ 08520
Made in India
Code .: TS/DRUGS/22/2009

Relabeled By: Preferred Pharmaceuticals Inc.

PACKAGE LABEL-PRINCIPAL DISPLAY PANEL - 2 mg Blister Carton (4 x 6's Tablets)

AUROHEALTH
Relabeled By: Preferred Pharmaceuticals Inc.
NDC 68788-8393
*Compare to the active
ingredient of Imodium® A-D
Loperamide Hydrochloride
Tablets USP 2 mg
Anti-Diarrheal
Controls the symptoms of diarrhea
24 Tablets